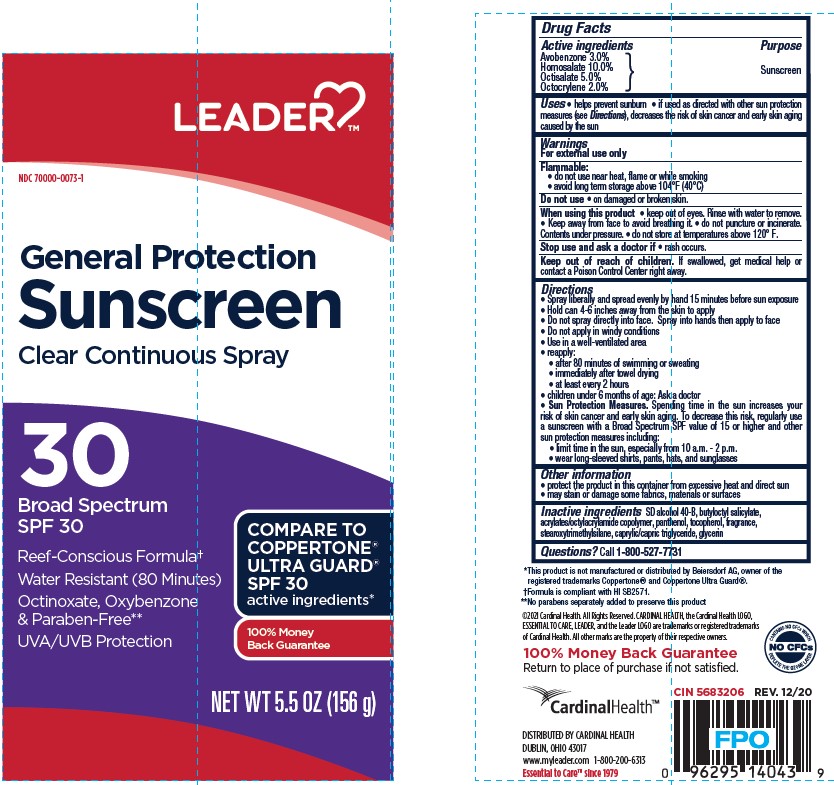 DRUG LABEL: Cardinal Health Leader General Protection Sunscreen SPF 30
NDC: 70000-0073 | Form: SPRAY
Manufacturer: CARDINAL HEALTH, INC.
Category: otc | Type: HUMAN OTC DRUG LABEL
Date: 20251202

ACTIVE INGREDIENTS: OCTISALATE 50 mg/1 g; AVOBENZONE 30 mg/1 g; HOMOSALATE 100 mg/1 g; OCTOCRYLENE 20 mg/1 g
INACTIVE INGREDIENTS: PANTHENOL; GLYCERIN; MEDIUM-CHAIN TRIGLYCERIDES; BUTYLOCTYL SALICYLATE; ACRYLATE/ISOBUTYL METHACRYLATE/N-TERT-OCTYLACRYLAMIDE COPOLYMER (75000 MW); ALCOHOL; STEAROXYTRIMETHYLSILANE; .ALPHA.-TOCOPHEROL, DL-

Cardinal Health Leader General Protection Sunscreen SPF 30 Clear Continious Spray

Active ingredients

Avobenzone 3.0%, Homosalate 10.0%, Octisalate 5.0%, Octocrylene 2.0%

Purpose

Sunscreen

Uses

• helps prevent sunburn • if used as directed with other sun protection measures (see Directions), decreases the risk of skin cancer and early skin aging caused by the sun

Warnings

For external use only

Flammable:

• do not use near heat, flame or while smoking

• avoid long term storage above 104°F (40°C)

Do not use

• on damaged or broken skin.

When using this product

• keep out of eyes. Rinse with water to remove.

• Keep away from face to avoid breathing it.

• do not puncture or incinerate.Contents under pressure.

• do not store at temperatures above 120° F.

Stop use and ask a doctor if

• rash occurs.

Keep out of reach of children.

If swallowed, get medical help or contact a Poison Control Center right away.

Directions

• Spray liberally and spread evenly by hand 15 minutes before sun exposure

• Hold can 4-6 inches away from the skin to apply

• Do not spray directly into face. Spray into hands then apply to face

• Do not apply in windy conditions

• Use in a well-ventilated area

reapply:

• after 80 minutes of swimming or sweating

• immediately after towel drying

• at least every 2 hours

• children under 6 months of age: Ask a doctor

Sun Protection Measures. Spending time in the sun increases your risk of skin cancer and early skin aging. To decrease this risk, regularly use a sunscreen with a Broad Spectrum SPF value of 15 or higher and other sun protection measures including:

• limit time in the sun, especially from 10 a.m. - 2 p.m.

• wear long-sleeved shirts, pants, hats, and sunglasses

Other information

• protect the product in this container from excessive heat and direct sun

• may stain or damage some fabrics, materials or surfaces

Inactive ingredients

SD alcohol 40-B, butyloctyl salicylate, acrylates/octylacrylamide copolymer, panthenol, tocopherol, fragrance, stearoxytrimethylsilane, caprylic/capric triglyceride, glycerin

Label

Cardinal Health Leader General Protection Sunscreen SPF 30 Clear Continious Spray

5.5 oz (156 g)

NDC 70000-0073-1